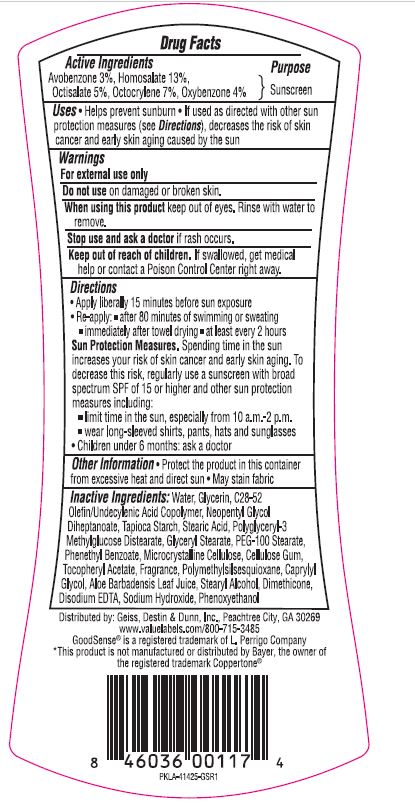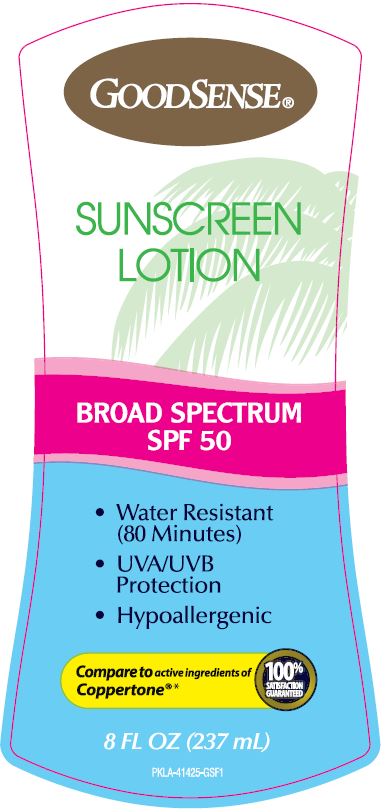 DRUG LABEL: GoodSense Sunscreen SPF 50
NDC: 70281-639 | Form: LOTION
Manufacturer: Solskyn Personal Care LLC
Category: otc | Type: HUMAN OTC DRUG LABEL
Date: 20190627

ACTIVE INGREDIENTS: AVOBENZONE 3 g/100 g; HOMOSALATE 13 g/100 g; OCTISALATE 5 g/100 g; OCTOCRYLENE 7 g/100 g; OXYBENZONE 4 g/100 g
INACTIVE INGREDIENTS: STARCH, TAPIOCA; POLYGLYCERYL-3 DISTEARATE; STEARYL ALCOHOL; DIMETHICONE; SODIUM HYDROXIDE; PHENOXYETHANOL; PHENETHYL BENZOATE; MICROCRYSTALLINE CELLULOSE; .ALPHA.-TOCOPHEROL ACETATE; POLYMETHYLSILSESQUIOXANE (4.5 MICRONS); CAPRYLYL GLYCOL; ALOE VERA LEAF; MAGNESIUM DISODIUM EDTA; WATER; GLYCERIN; STEARIC ACID; UNDECYLENIC ACID; NEOPENTYL GLYCOL; GLYCERYL STEARATE/PEG-100 STEARATE; CARBOXYMETHYLCELLULOSE SODIUM, UNSPECIFIED FORM

GoodSense Sunscreen SPF 50

Active Ingredients

Avobenzone 3%

Homosalate 13%

Octisalate 5%

Octocrylene 7%

Oxybenzone 4%

Purpose

Sunscreen

Use

• Helps prevent sunburn • If used as directed with other sun protection measures (see Directions), decreases the risk of skin cancer and early skin aging caused by the sun

Warnings

• For external use only

• Do not use on damaged or broken skin.

• When using this product keep out of eyes. Rinse with water to remove.

Stop use and ask a doctor if rash occurs.

• Keep out of reach of children. If swallowed, get medical help or contact a Poison Control Center right away.

Directions

• Apply liberally 15 minutes before sun exposure

• Re-apply: ■ after 80 minutes of swimming or sweating

■ immediately after towel drying ■ at least every 2 hours

Sun Protection Measures. Spending time in the sun increases your risk of skin cancer and early skin aging. To decrease this risk, regularly use a sunscreen with broad spectrum SPF of 15 or higher and other sun protection measures including:

■ limit time in the sun, especially from 10 a.m.-2 p.m.

■ wear long-sleeved shirts, pants, hats and sunglasses

• Children under 6 months: ask a doctor

Other information

• Protect the product in this container from excessive heat and direct sun • May stain fabric

Inactive Ingredients:

Water, Glycerin, C28-52 Olefin/Undecylenic Acid Copolymer, Neopentyl Glycol Diheptanoate, Stearic Acid, Polyglyceryl-3 Methylglucose Distearate, Tapioca Starch, Glyceryl Stearate, PEG-100 Stearate, Microcrystalline Cellulose, Phenethyl Benzoate, Cellulose Gum, Tocopheryl Acetate, Fragrance, Polymethylsilsesquioxane, Caprylyl Glycol, Aloe Barbadensis Leaf Juice, Stearyl Alcohol, Dimethicone, Disodium EDTA, Sodium Hydroxide, Phenoxyethanol

Questions

Distributed by: Geiss, Destin & Dunn, Inc, Peachtree City, GA 30269

www.valuelabels.com/800-715-3485

GoodSense is a registered trademark of L. Perrigo Company

*This product is not manufactured or distributed by Bayer, the owner of the registered trademark Coppertone

Principal Display Panel

GOODSENSE

SUNSCREEN

LOTION

BROAD SPECTRUM

SPF 50

• Water Resistant

(80 Minutes)

• UVA/UVB Protection

• Hypoallergenic

Compare to active ingredients of

Coppertone

100%

Satisfaction

Guaranteed

8 FL OZ (237 mL)

PKLA-41425-GFS1